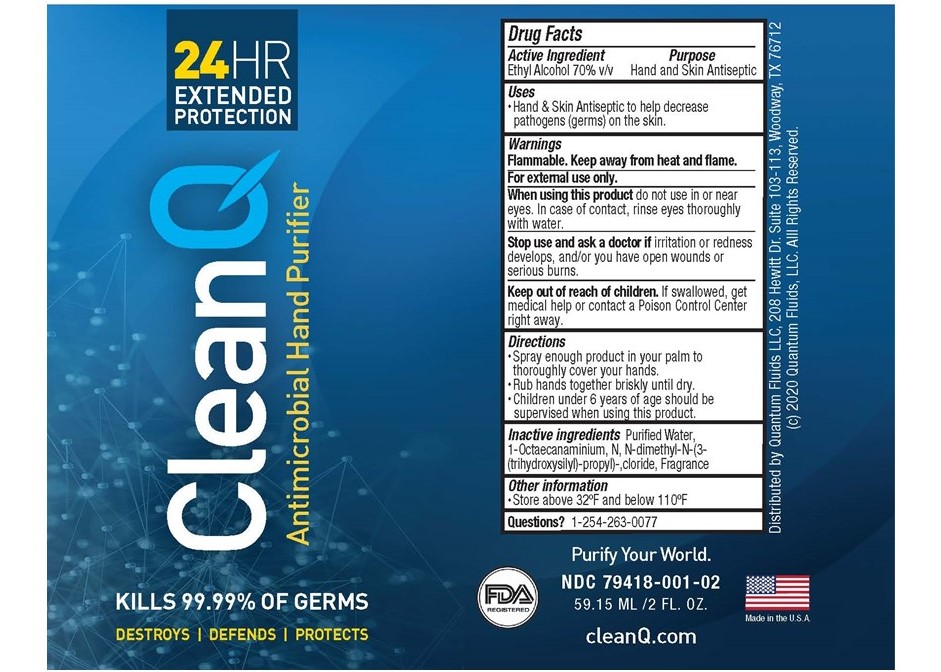 DRUG LABEL: CleanQ Antimicrobial Hand Purifier
NDC: 79418-001 | Form: LIQUID
Manufacturer: Quantum Fluids LLC
Category: otc | Type: HUMAN OTC DRUG LABEL
Date: 20200702

ACTIVE INGREDIENTS: ALCOHOL 70 mL/100 mL
INACTIVE INGREDIENTS: WATER; OCTADECYLDIMETHYL(3-TRIHYDROXYSILYLPROPYL)AMMONIUM CHLORIDE

Drug Facts

Active ingredient

Ethyl Alcohol 70%

Purpose

Hand & Skin Antiseptic

Uses

Hand & Skin Antiseptic to help decrease pathogens (germs) on the skin.

Warnings

For external use only.

Flammable. Keep away from heat and flame.

*Do not use in or near eyes. In case of contact, rinse eyes thoroughly with water.

ASK DOCTOR

If irritation or redness develops, and/or you have open wounds or serious burns.

STOP USE

* If irritation or redness develops

* Have open wounds or serious burns

KEEP OUT OF REACH OF CHILDREN

If swallowed, get medical help or contact a Poison Control Center right away.

DOSAGE AND ADMINISTRATION

* Spray enough product in your palm to thoroughly cover your hands.

* Rub hands together briskly until dry.

* Children under 6 years of age should be supervised when using this product.

INACTIVE INGREDIENT

Purified water, 1-Octaecanaminium,N,N-dimethyl-N-(3-trihydroxysilyl)-propyl)-cloride, Fragrance

PACKAGE LABEL

CleanQ Antimicrobial Hand Purifier

24HR Extended Protection

Kills 99.99% of Germs

Destroys/Defends/Protects

Purify Your World

Distributed by:

Quantum Fluids LLC, 208 Hewitt Dr. Suite 103-113, Woodaway, TX 76712

(c)2020 Quantum Fluids, LLC. All Rights Reserved.

xx oz (zzzml) NDC 79418-001-xx